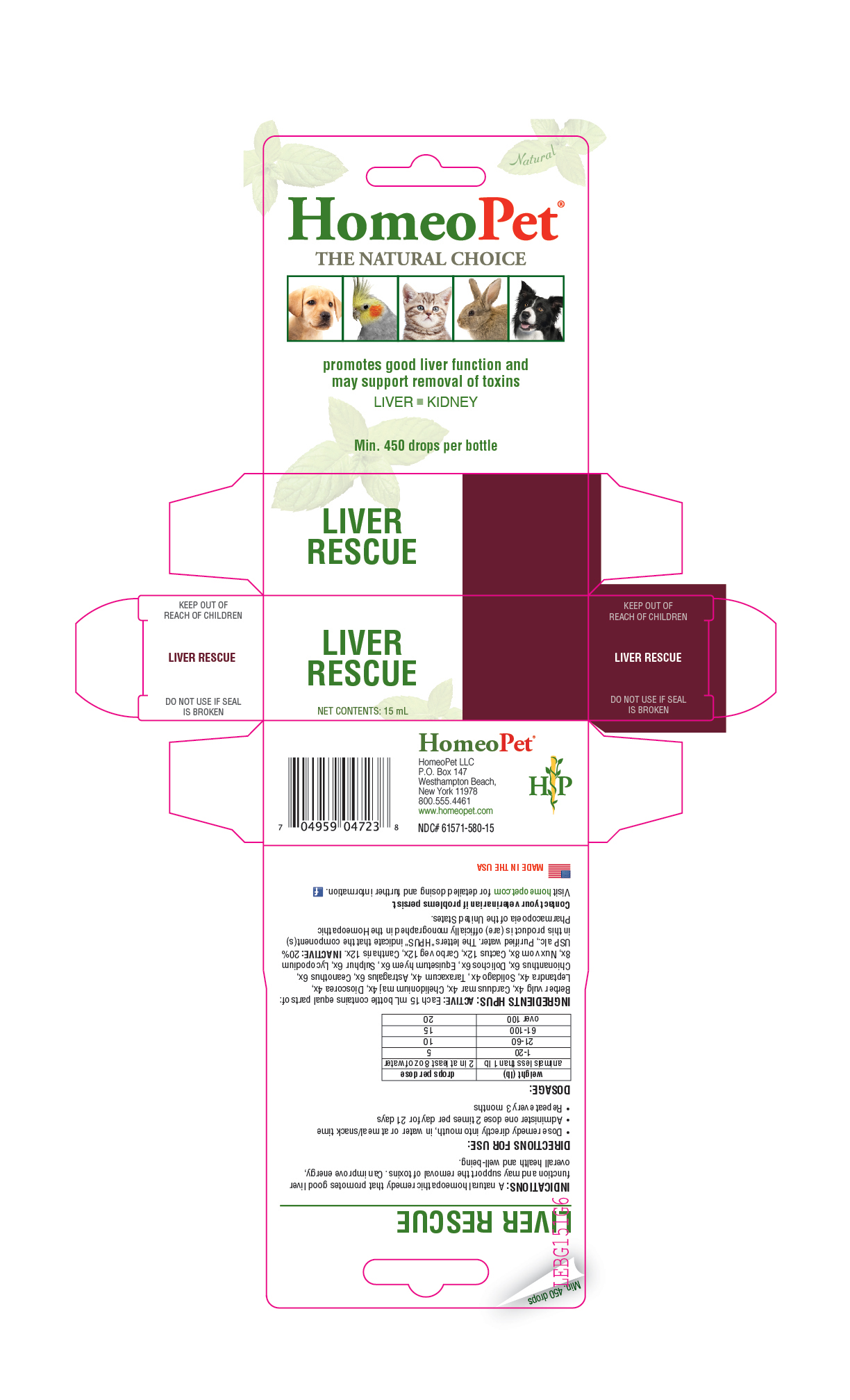 DRUG LABEL: Liver Rescue
NDC: 61571-580 | Form: LIQUID
Manufacturer: HomeoPet, LLC
Category: homeopathic | Type: OTC ANIMAL DRUG LABEL
Date: 20201029

ACTIVE INGREDIENTS: ASTRAGALUS NUTTALLII LEAF 6 [hp_X]/15 mL; BERBERIS VULGARIS ROOT BARK 4 [hp_X]/15 mL; SELENICEREUS GRANDIFLORUS STEM 12 [hp_X]/15 mL; LYTTA VESICATORIA 12 [hp_X]/15 mL; ACTIVATED CHARCOAL 12 [hp_X]/15 mL; SILYBUM MARIANUM SEED 4 [hp_X]/15 mL; CEANOTHUS AMERICANUS LEAF 6 [hp_X]/15 mL; CHELIDONIUM MAJUS 4 [hp_X]/15 mL; CHIONANTHUS VIRGINICUS BARK 6 [hp_X]/15 mL; DIOSCOREA VILLOSA ROOT 4 [hp_X]/15 mL; MUCUNA PRURIENS FRUIT TRICHOME 6 [hp_X]/15 mL; EQUISETUM HYEMALE 6 [hp_X]/15 mL; CULVER'S ROOT 4 [hp_X]/15 mL; LYCOPODIUM CLAVATUM SPORE 8 [hp_X]/15 mL; STRYCHNOS NUX-VOMICA SEED 8 [hp_X]/15 mL; SULFUR 6 [hp_X]/15 mL; SOLIDAGO VIRGAUREA FLOWERING TOP 4 [hp_X]/15 mL; TARAXACUM OFFICINALE 4 [hp_X]/15 mL
INACTIVE INGREDIENTS: ALCOHOL; WATER

Liver Rescue

PURPOSE

Promotes good liver function and may support removal of toxins

LIVER - KIDNEY

DOSAGE AND ADMINISTRATION

- Dose remedy directly into mouth, in water or on food

- Administer one dose 2 times per day for 21 days

- Repeat every 3 months

weight (lb) | drops per dose
animals less than 1 lb | 2 in at least 8 oz of water
1-20 | 5
21-60 | 10
61-100 | 15
over 100 | 20

ASK DOCTOR

Contact Veterinarian if problems persist.

Visit homeopet.com for detailed dosing and further information.

INGREDIENTS HPUS: ACTIVE

Each 15 mL bottle contains equal parts of: Berber vulg 4x, Carduus mar 4x, Chelidonium maj 4x, Dioscorea 4x, Leptandra 4x, Solidago 4x, Taraxacum 4x, Astragalus 6x, Ceanothus 6x, Chionanthus 6x, Dolichos 6x, Equisetum hyem 6x, Sulphur 6x, Lycopodium 8x, Nux vom 8x, Cactus 12x, Carbo veg 12x, Cantharis 12x.

INACTIVE

Alcohol, Purified Water

INDICATIONS

A natural homeopathic remedy that promotes good liver function and may support the removal of toxins. Can improve energy, overall health and well-being.